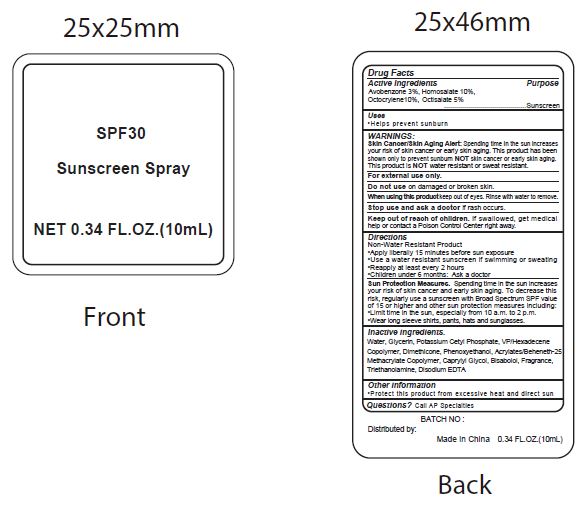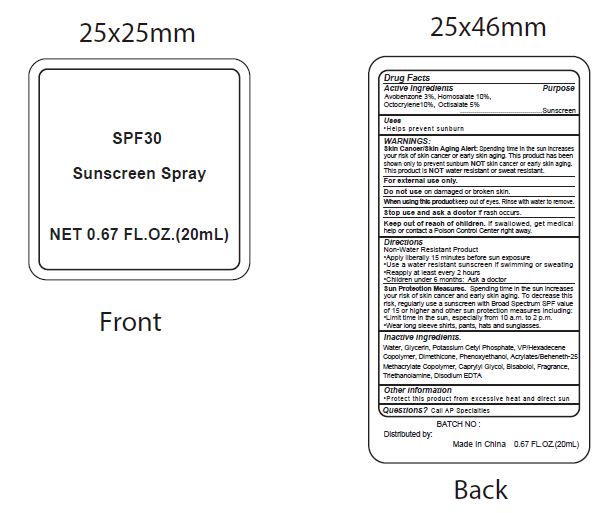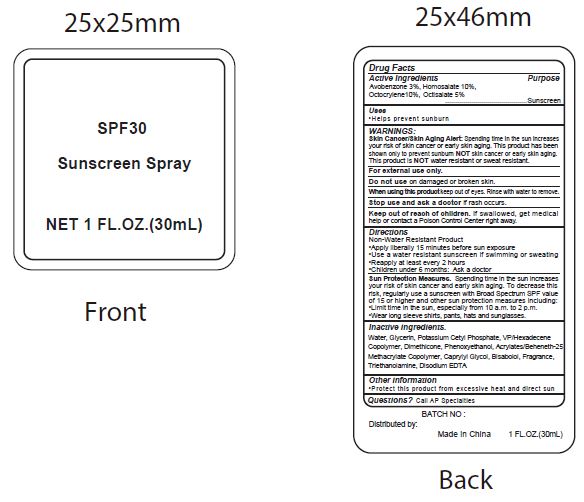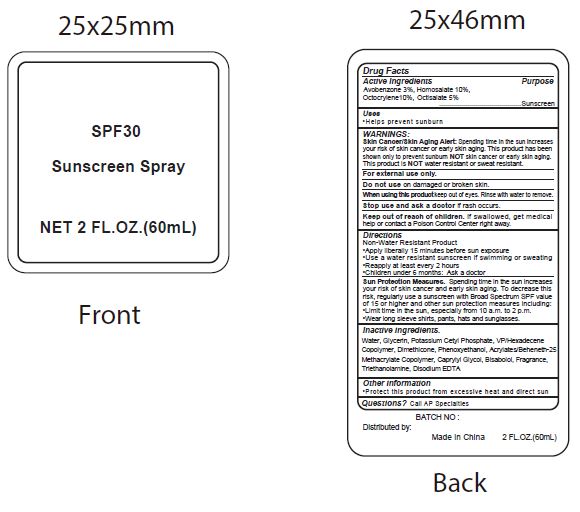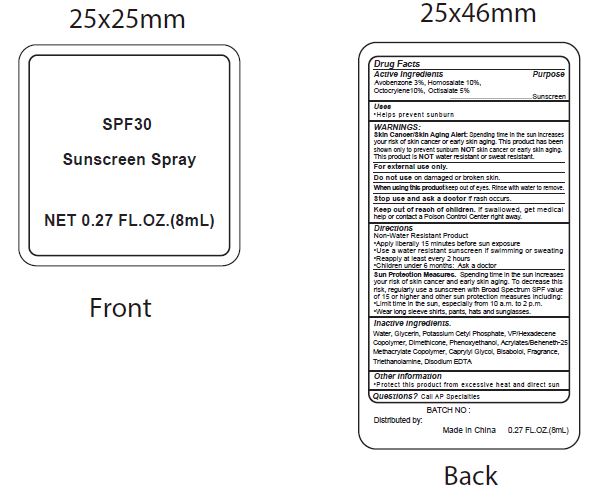 DRUG LABEL: SPF30 Sunscreen
NDC: 70412-238 | Form: SPRAY
Manufacturer: Zhejiang Ayan Biotech Co., Ltd.
Category: otc | Type: HUMAN OTC DRUG LABEL
Date: 20231106

ACTIVE INGREDIENTS: AVOBENZONE 30 mg/1 mL; HOMOSALATE 100 mg/1 mL; OCTOCRYLENE 100 mg/1 mL; OCTISALATE 50 mg/1 mL
INACTIVE INGREDIENTS: WATER; GLYCERIN; POTASSIUM CETYL PHOSPHATE; CETOSTEARYL ALCOHOL; DIMETHICONE; CAPRYLYL GLYCOL; PHENOXYETHANOL; GLYCERYL MONOSTEARATE; VINYLPYRROLIDONE/HEXADECENE COPOLYMER; LEVOMENOL; CARBOXYPOLYMETHYLENE; TROLAMINE; EDETATE DISODIUM ANHYDROUS; COCONUT

SPF30 Sunscreen Spray

Active Ingredients

Avobenzone 3%, Homosalate 10%, Octocrylene 10%, Octisalate 5%

Purpose

Sunscreen

Uses

- Helps prevent sunburn

WARNINGS:

Spending time in the sun increases your risk of skin cnacer or early skin aging. this product has been shown only to prevent sunburn skin cancer or early skin aging. this product is water resistant or sweat resistant. Skin Cancer/Skin Aging Alert: NOTNOT

For external use only.

Do not use on damaged or broken skin.

When using this product keep out of eyes. Rinse with water to remove.

Stop use and ask a doctor if rash occurs.

Keep out of reach of children.

If swallowed, get medical help or contact a Poison Control Center right away.

Directions

Non-Water Resistant Product

- Apply liberally 15 minutes before sun exposure
- Use a water resistant sunscreen if swimming or sweating
- Reapply at least every 2 hours
- Children under 6 months: Ask a doctor

inactive ingredients.

Water, Glycerin, Potassium Cetyl Phosphate, VP/Hexadecene Copolymer, Dimethicone, Phenoxyethanol, Acrylates/Beheneth-25 Methacrylate Copolymer, Caprylyl Glycol, Bisabolol, Fragrance, Triethanolamine, Disodium EDTA